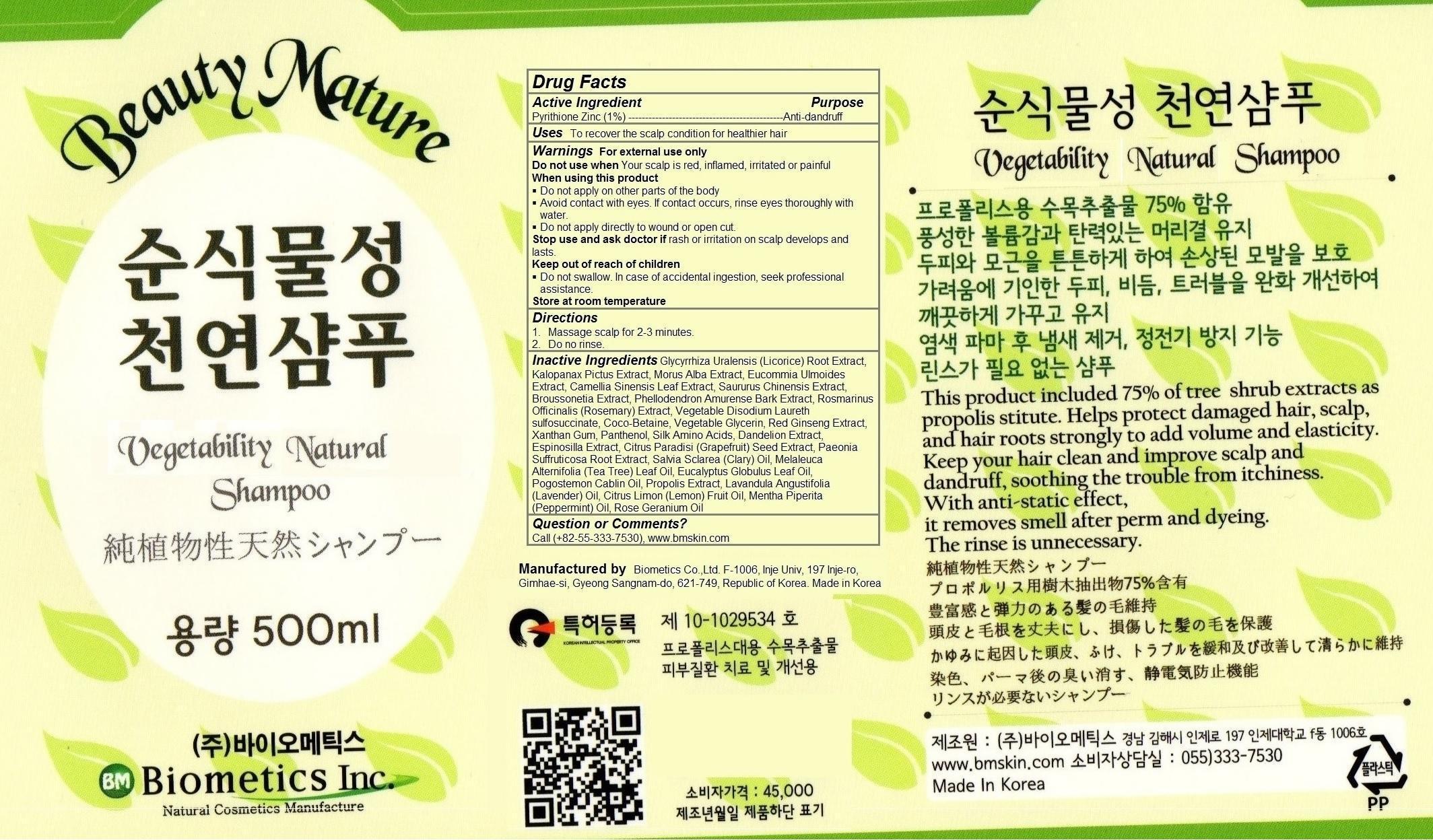 DRUG LABEL: Vegetability Natural
NDC: 62818-100 | Form: SHAMPOO
Manufacturer: Biometics Co.,Ltd.
Category: otc | Type: HUMAN OTC DRUG LABEL
Date: 20140413

ACTIVE INGREDIENTS: Pyrithione Zinc 5 g/500 g
INACTIVE INGREDIENTS: GLYCYRRHIZA URALENSIS WHOLE; KALOPANAX SEPTEMLOBUS BARK; MORUS ALBA WHOLE; EUCOMMIA ULMOIDES WHOLE; CAMELLIA SINENSIS WHOLE; SAURURUS CHINENSIS WHOLE; BROUSSONETIA KAZINOKI WHOLE; Phellodendron Amurense Bark; ROSMARINUS OFFICINALIS WHOLE; DISODIUM LAURETH SULFOSUCCINATE; Coco-Betaine; GLYCERIN; ASIAN GINSENG; Xanthan Gum; Panthenol; AMINO ACIDS, SILK; DANDELION HONEY; CITRUS PARADISI SEED; PAEONIA SUFFRUTICOSA ROOT BARK; SALVIA SCLAREA SEED OIL; MELALEUCA ALTERNIFOLIA LEAF; EUCALYPTUS GLOBULUS LEAF; POGOSTEMON CABLIN WHOLE; PROPOLIS WAX; LAVANDULA ANGUSTIFOLIA WHOLE; CITRUS LIMON FRUIT OIL; MENTHA PIPERITA; GERANIUM OIL, ALGERIAN TYPE

Vegetability Natural Shampoo